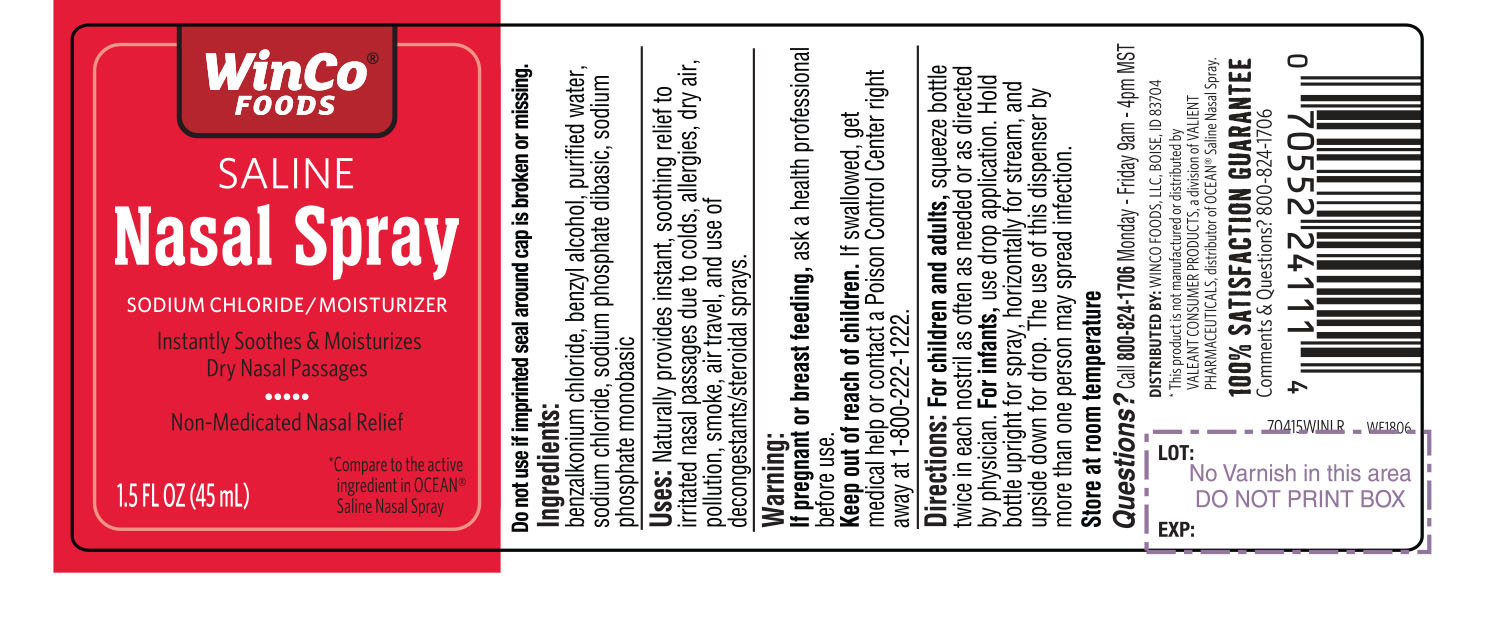 DRUG LABEL: WinCo Foods Saline Nasal Relief
NDC: 67091-327 | Form: SPRAY
Manufacturer: WinCo Foods, LLC
Category: otc | Type: HUMAN OTC DRUG LABEL
Date: 20180802

ACTIVE INGREDIENTS: SODIUM CHLORIDE .65 g/100 mL
INACTIVE INGREDIENTS: BENZALKONIUM CHLORIDE; BENZYL ALCOHOL; WATER; SODIUM PHOSPHATE, DIBASIC; SODIUM PHOSPHATE, MONOBASIC

WinCo® FOODS SALINE Nasal Spray Sodium Chloride 1.5 FL OZ (45 mL)

ACTIVE INGREDIENT

Ingredients

benzalkonium chloride, benzyl alcohol, purified water, sodium chloride, sodium phosphate dibasic, sodium phosphate monobasic,

Uses

Naturally provides instant, soothing relief to irritated nasal passages due to colds, allergies, dry air, pollution, smoke, air travel, and use of decongestants/steroidal sprays.

Warnings

If pregnant or breast feeding, ask a health professional before use.

Keep out of reach of children, if swallowed, get medical help or contact a Poison Control Center right away at 1-800-222-1222.

Directions:

For children and adults, squeeze bottle twice in each nostril as often as needed or as directed by physician.

For Infants,

use drop application. Hold bottle upright for spray, horizontally for stream, and upside down for drop.

The use of this dispenser by more than one person may spread infection.

Store at room temperature

Click here to enter text.

[Enter Inactive Ingredients here]

Questions

Call 800-824-1706

Call 800-824-1706

Monday-Friday 9am-4pm MST

DOSAGE AND ADMINISTRATION

WinCo® Foods

Saline Nasal Spray

Sodium Chloride / Moisturizer

Instantly Soothes & Moisturizes

Dry Nasal Passages

Non –Medicated Nasal Relief

1.5FL OZ (45 mL)

*Compare to the active ingredient in OCEAN® Saline Nasal Spray

DISTRIBUTED BY:

WINCO FOODS, LLC,

BOISE, ID 83704

Do not use if imprinted seal around cap is broken or missing,

*This product is not manufactured or distributed by VALEANT CONSUMER PRODUCTS, a division of VALEANT PHARMACEUTICALS, distributor of OCEAN® saline Nasal Spray.

100% SATIFACTION GUARANTEE

Comments & Questions? 800-824-1706